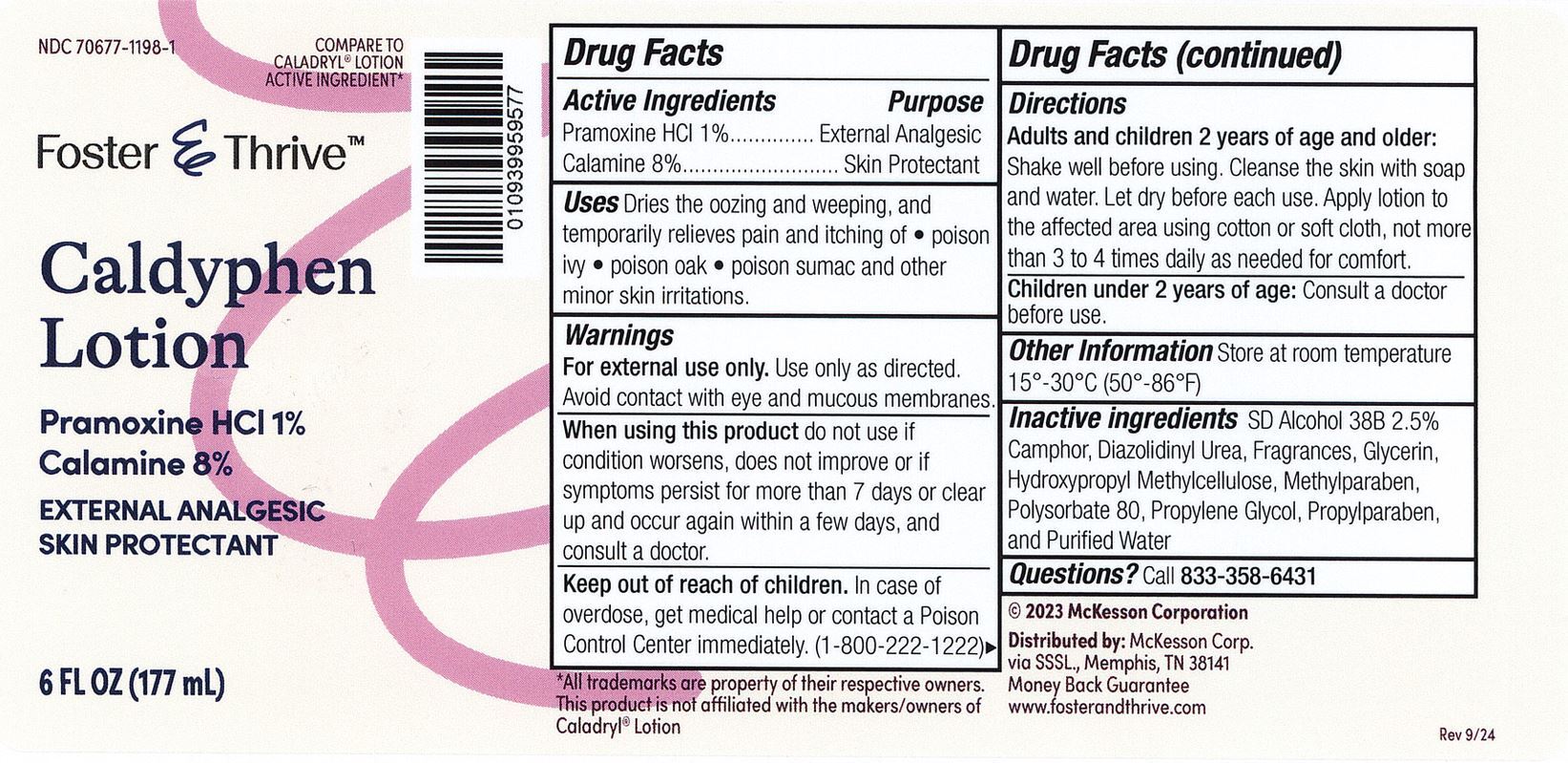 DRUG LABEL: Foster and Thrive Caldyphen
NDC: 70677-1198 | Form: LOTION
Manufacturer: Strategic Sourcing Services, LLC
Category: otc | Type: HUMAN OTC DRUG LABEL
Date: 20241218

ACTIVE INGREDIENTS: ZINC OXIDE 80 mg/1 mL; PRAMOXINE HYDROCHLORIDE 10 mg/1 mL
INACTIVE INGREDIENTS: CAMPHOR (NATURAL); DIAZOLIDINYL UREA; GLYCERIN; HYPROMELLOSE, UNSPECIFIED; METHYLPARABEN; POLYSORBATE 80; PROPYLENE GLYCOL; PROPYLPARABEN; WATER

Foster & Thrive Caldyphen Lotion

Drug Facts

Active Ingredients

Calamine 8%

Pramoxine HCl 1%

Purpose

Skin Protectant

External analgesic

Uses

Dries the oozing and weeping, and temporarily relieves pain and itching of poison ivy, oak, and sumac or other skin irritations.

Warnings

For external use only. Use only as directed.

When using this product. Avoid contact with eyes and moucous membranes.

When using this product

do not use if condition worsens, does not improve or if symptoms persist for more than 7 days or clear up and occur again within a few days, and consult a doctor.

Keep out of reach of children.

In case of accidental ingestion, seek profesional assistance or contact a Poison Control Center immediately. (1-800-222-1222)

Directions

Adults and children 2 yr. of age and older. Shake well before using. Cleanse the skin with soap and water and let dry. Apply to the affected area using cotton or soft cloth, not more than 3 to 4 times daily as needed for comfort.

Children under 2 yrs. of age. Consult a doctor before use.

Inactive Ingredients

SD Alcohol 38B 2.5%, Camphor, Diazolidinyl Urea, Fragrances, Glycerin, Hydroxypropyl Methycelulose, Methylparaben, Polysorbate 80, Propylene Glycol, Propylparaben and Purified Water.

Other information

Store at room temperature 15-30C (59-86F)

Distributed by: McKesson Corp.

SSSL., Memphis, TN 38141

Questions?

Call 833-358-6431